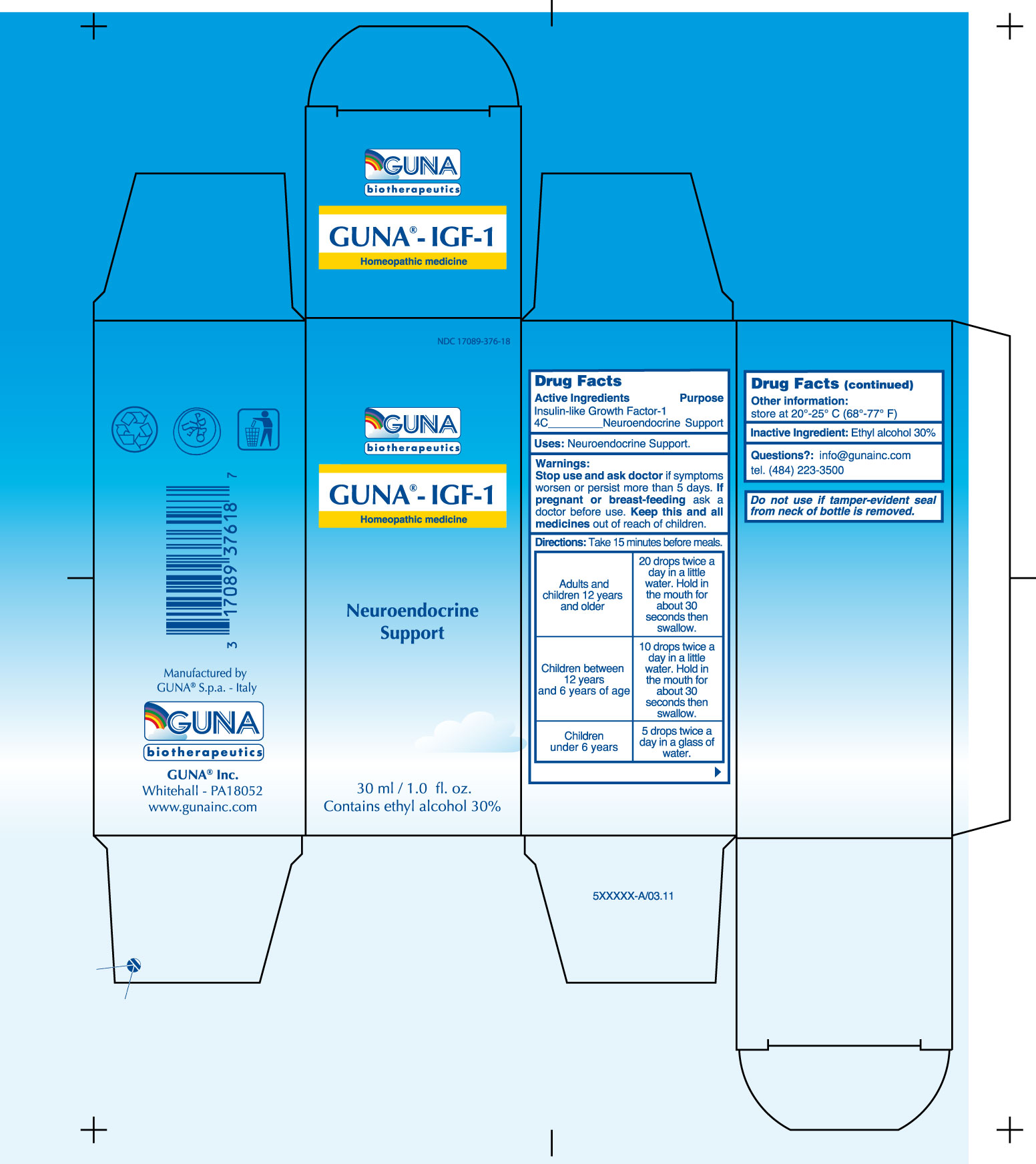 DRUG LABEL: GUNA-IGF
NDC: 17089-376 | Form: SOLUTION/ DROPS
Manufacturer: Guna spa
Category: homeopathic | Type: HUMAN OTC DRUG LABEL
Date: 20221115

ACTIVE INGREDIENTS: MECASERMIN 4 [hp_C]/30 mL
INACTIVE INGREDIENTS: ALCOHOL 9 mL/30 mL

GUNA-IGF 1

ACTIVE INGREDIENT

INSULIN-LIKE GROWTH FACTOR-1 4C

PURPOSE

Neuroendocrine Support

KEEP OUT OF REACH OF CHILDREN

Keep this and all medicines out of reach of children

INDICATIONS & USAGE

Neuroendocrine Support

WARNINGS

Stop use and ask doctor if symptoms worsen or persist more than 5 days

DIRECTIONS

Take 15 minutes before meals.
Adults and children 12 years and older 20 drops twice a day in a little water. Hold in the mouth for about 30 seconds then swallow.
Children between 12 years and 6 years of age 10 drops twice a day in a little water. Hold in the mouth for about 30 seconds then swallow.
Children under 6 years 5 drops twice a day in a glass of water.

INACTIVE INGREDIENT

Ethyl Alcohol 30%